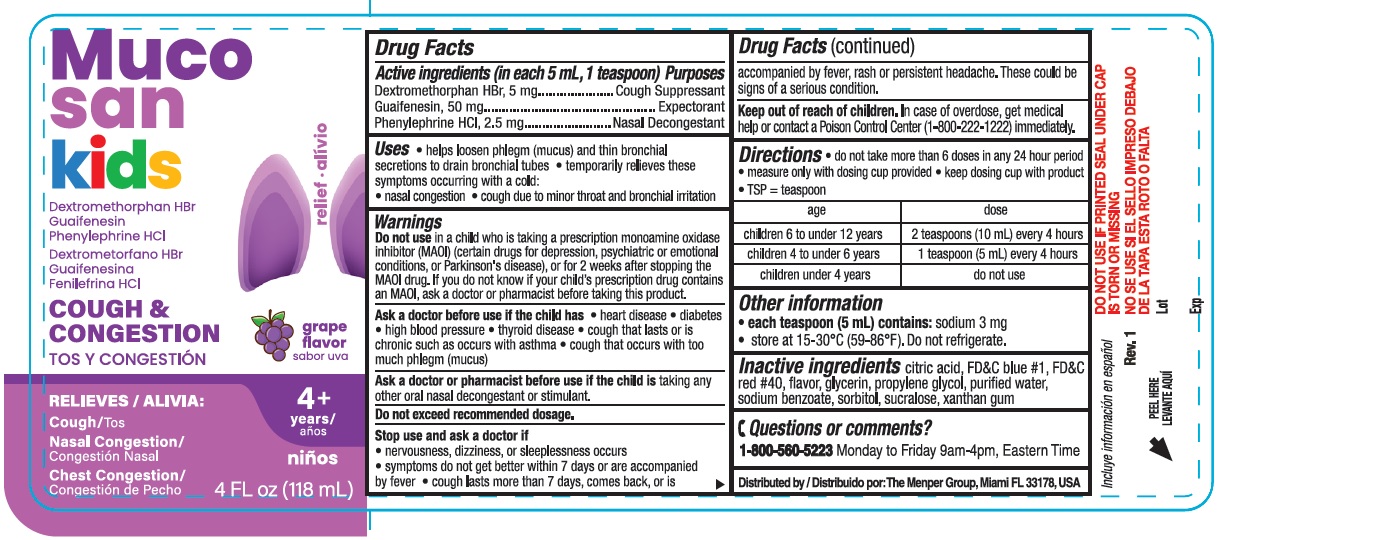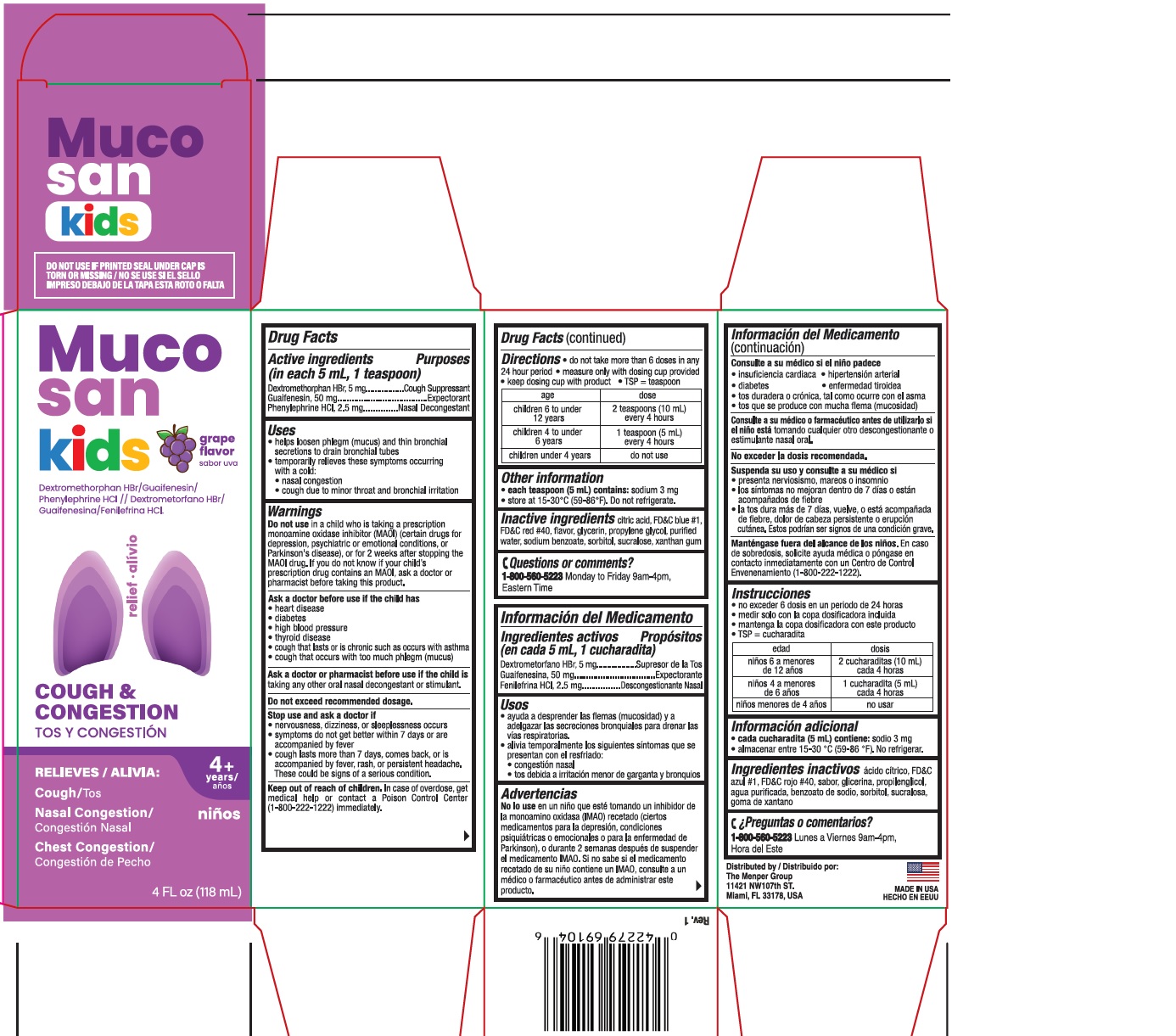 DRUG LABEL: Mucosan Childrens Multi-Symptom Grape
NDC: 53145-691 | Form: LIQUID
Manufacturer: Menper Distributors, Inc.
Category: otc | Type: HUMAN OTC DRUG LABEL
Date: 20260108

ACTIVE INGREDIENTS: GUAIFENESIN 50 mg/5 mL; DEXTROMETHORPHAN HYDROBROMIDE 5 mg/5 mL; PHENYLEPHRINE HYDROCHLORIDE 2.5 mg/5 mL
INACTIVE INGREDIENTS: CITRIC ACID; XANTHAN GUM; SODIUM BENZOATE; FD&C RED NO. 40; WATER; FD&C BLUE NO. 1; GLYCERIN; SORBITOL; SUCRALOSE; PROPYLENE GLYCOL

Mucosan Childrens Multi-Symptom Grape

ACTIVE INGREDIENT

Active ingredients (in each 5 mL, 1 teaspoon) Purposes

Dextromethorphan HBr, 5 mg...............................Cough suppressant

Guaifenesin, 50 mg...............................................Expectorant

Phenylephrine HCl, 2.5 mg...................................Nasal decongestant

Purpose

Cough suppressant

Expectorant

Nasal decongestant

Uses

- helps loosen phlegm (mucus) and thin bronchial secretions to drain bronchial tubes
- temporarily relieves these symptoms occurring with a cold:
- nasal congestion
- cough due to minor throat and bronchial irritation

WARNINGS

Do not usein a child who is taking a prescription monoamine oxidase inhibitor (MAOI) (certain drugs for depression, psychiatric or emotional conditions, or Parkinson's disease), or for 2 week after stopping the MAOI drug. If you do not know if your child's prescritpion drug contains an MAOI, ask a doctor or pharmacist before taking this product.

Ask a doctor before use if the child has

- heart disease
- diabetes
- high blood pressure
- thyroid disease
- cough that lasts or is chronic such as occurs with asthma
- cough that occurs with too much phlegm (mucus)

Ask a doctor or pharmacist before use if the child istaking any other oral nasal decongestant or stimulant.

OVERDOSAGE

Do not exceed recommended dosage.

Stop use and ask a doctor if

- nervousness, dizziness, or sleeplessness occurs
- symptoms do not get better within 7 days or are accompanied by fever
- cough lasts more than 7 days, comes back, or is accompanied by fever, rash, or persistent headache.

These could be signs of a serious condition.

Keep out of reach of children.In case of overdose, get medical help or contact a Poison Control Center (1-800-222-1222) immediately.

Directions

- do not take more than 6 doses in any 24 hour period
- measure only with dosing cup provided
- keep dosing cup with product
- TSP=teaspoon

age | dose
children 6 to under 12 years | 2 teaspoons (10mL) every 4 hours
children 4 to under 6 years | 1 teaspoon (5mL) every 4 hours
children under 4 years | do not use

Other information

- each teaspoon (5mL) contains:sodium 3 mg
- store at 15-30°C (59-86°F). Do not refrigerate.

Inactive ingredients

citric acid, FD&C blue #1, FD&C red #40, flavor, glycerin, propylene glycol, purified water, sodium benzoate, sorbitol, sucralose, xanthan gum.

Questions or comments?

1-800-560-5223 Monday to Friday 9am-4pm, Eastern Time